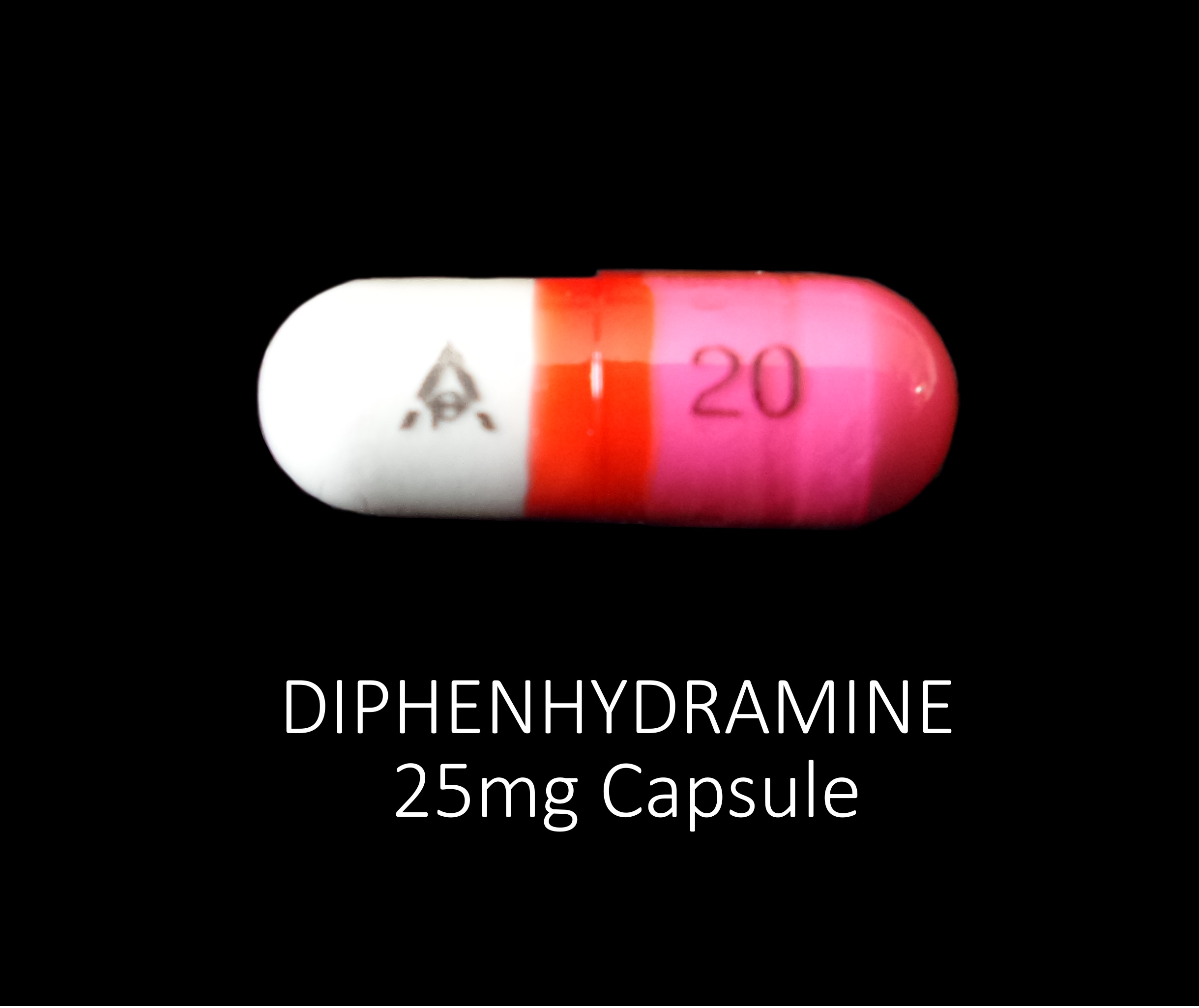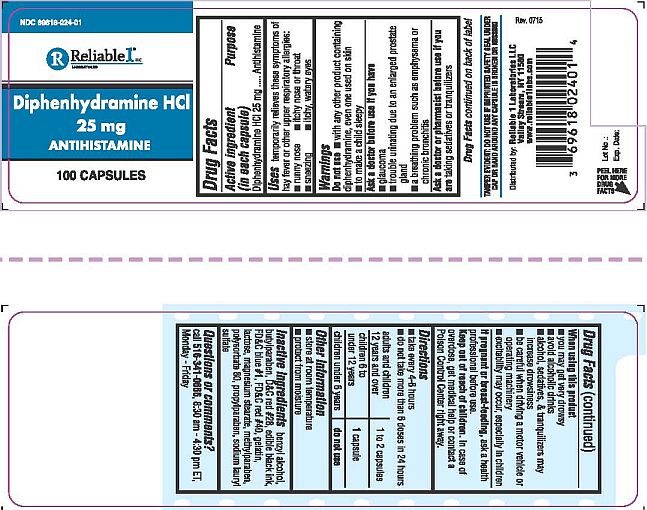 DRUG LABEL: Diphenhydramine HCl  25 mg
NDC: 69618-024 | Form: CAPSULE
Manufacturer: Reliable 1 Laboratories LLC
Category: otc | Type: HUMAN OTC DRUG LABEL
Date: 20250115

ACTIVE INGREDIENTS: DIPHENHYDRAMINE HYDROCHLORIDE 25 mg/1 1
INACTIVE INGREDIENTS: D&C RED NO. 28; METHYLPARABEN; SODIUM LAURYL SULFATE; GELATIN; POLYSORBATE 80; PROPYLPARABEN; BENZYL ALCOHOL; BUTYLPARABEN; FD&C BLUE NO. 1; FD&C RED NO. 40; LACTOSE; MAGNESIUM STEARATE

Diphenhydramine HCL 25 mg Capsules

Active ingredient (in each capsule)

Diphenhydramine HCL 25 mg

Purpose

Antihistamine

Uses

temporarily releaves these symptoms of hay fever or other upper respiratory allergies:

- runny nose
- itchy nose or throat
- sneezing
- itchy, watery eyes

Warnings

Do not use

- with any otherprodcut containing diphenhydramine, even one use on skin
- to make a child sleepy

Ask a doctor before use if you have

- glaucoma
- trouble urinating due to an enlarged prostate gland
- a breathing problem such as emphysema or chronic bronchitis

Ask a doctor or pharamcist before use if you are taking sedatives or tranquilizers

Drug Facts continued of back of label

When using this product

- you may get very drowsy
- avoid alcoholic drinks
- alcohol, sedatives, & tranquilizers may increase drowsiness
- be careful when driving a motor vehicle or operating machinery
- excitability may occur, especially in children

PREGNANCY OR BREAST FEEDING

If pregnant or breast-feeding, ask a health professional before use.

Keep out of reach of children. In case of overdose, get medical help or contact a Poison Control Center right away.

Directions

- take every 4-6 hours
- do not take more than 6 doses in 24 hours

adults and children 12 years and over | 1 to 2 capsules
children 6 to under 12 years | 1 capsule
children under 6 years | do not use

Other information

- store at room temperature
- protect from moisture

Inactive ingredients

benzl alcohol, butylparaben, D&C red #28, edible black ink, FD&C blue #1, FD&C red #40, gelatin, lactose, magnesium stearate, methlyparaben, polysorbate 80, propylparaben, sodium lauryl sulfate

Questions or comments?

call 516-341-0666, 8:30 am - 4:30 pm ET, Monday - Friday

TAMPER EVIDENT: DO NOT USE IF IMPRINTED SAFETY SEAL UNDER CAP OR BAND AROUND ANY CAPSULE IS BROKEN OR MISSING

Distributed by: Reliable 1 Laboratories LLC

Valley Stream, NY 11580

www.reliable1labs.com

Drug Facts

PACKAGE LABEL

NDC 69618-024-01

Diphenhydramine HCL 25 mg

ANTIHISTAMINE

100 CAPSULES